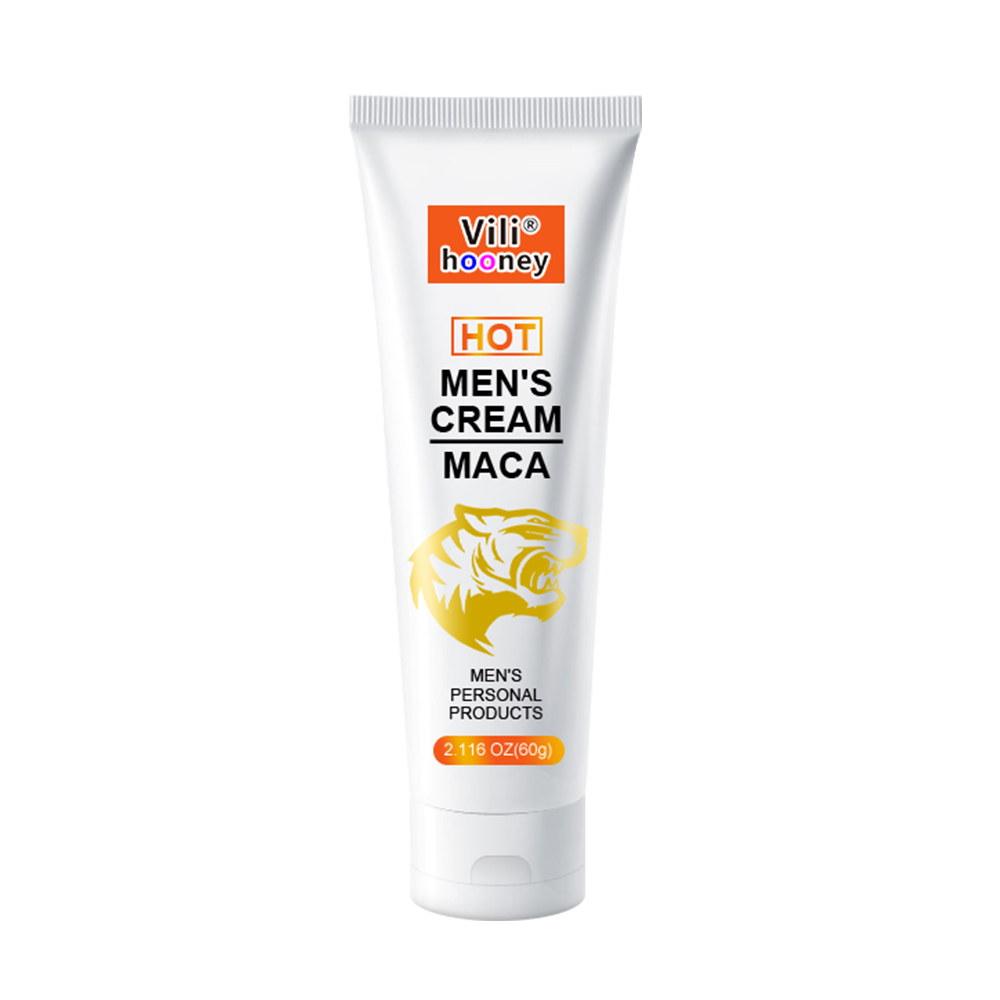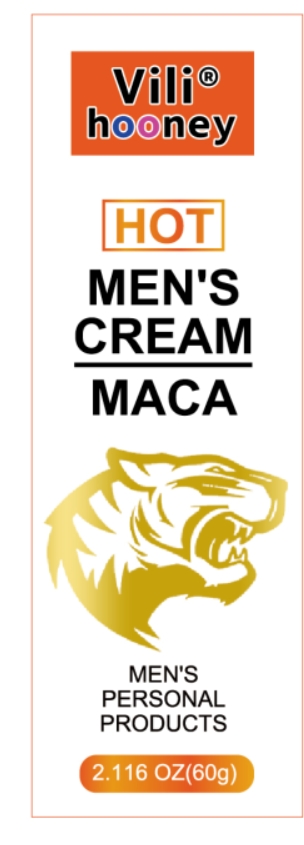 DRUG LABEL: Mens Massage Cream
NDC: 84025-092 | Form: CREAM
Manufacturer: Guangzhou Yanxi Biotechnology Co.. Ltd
Category: otc | Type: HUMAN OTC DRUG LABEL
Date: 20240726

ACTIVE INGREDIENTS: GLYCERIN 5 mg/60 g; PANTHENOL 3 mg/60 g
INACTIVE INGREDIENTS: WATER

DOSAGE AND ADMINISTRATION

For daily skin care

WARNINGS

Keep out of children

INACTIVE INGREDIENT

Aqua

INDICATIONS AND USAGE

Suitable for men's daily skin care

Keep out of children

PURPOSE

Cleanses and moisturizes men's skin